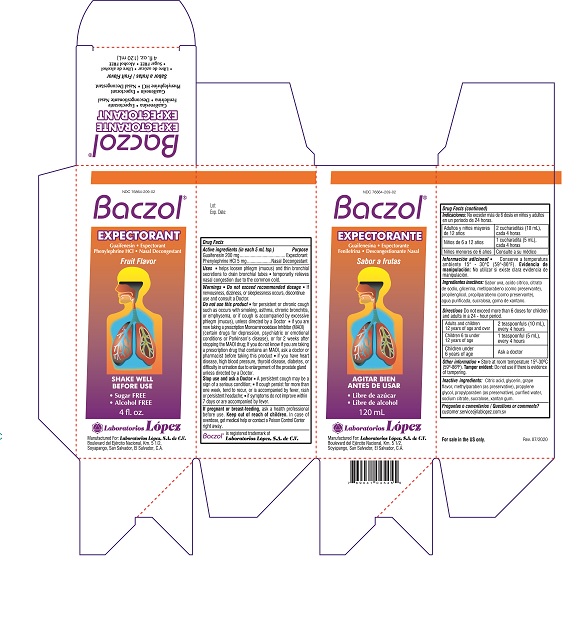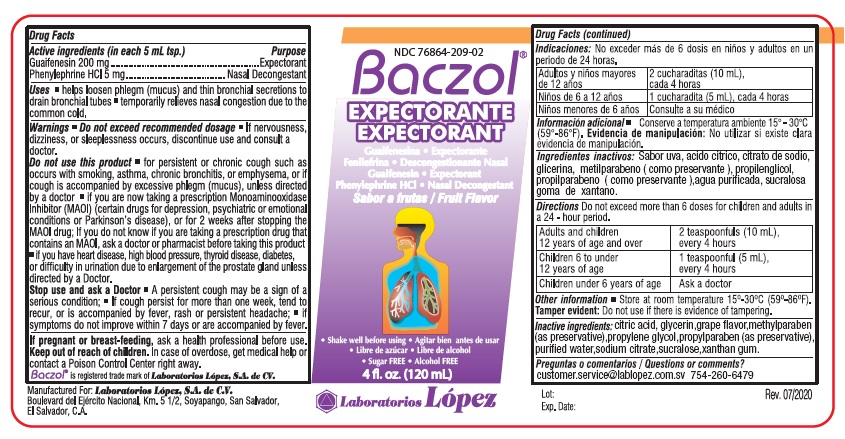 DRUG LABEL: BACZOL EXPECTORANT
NDC: 76864-209 | Form: SYRUP
Manufacturer: Procaps S.A. de C.V.
Category: otc | Type: HUMAN OTC DRUG LABEL
Date: 20241227

ACTIVE INGREDIENTS: GUAIFENESIN 200 mg/5 mL; PHENYLEPHRINE HYDROCHLORIDE 5 mg/5 mL
INACTIVE INGREDIENTS: CITRIC ACID MONOHYDRATE; GLYCERIN; METHYLPARABEN; PROPYLENE GLYCOL; PROPYLPARABEN; WATER; SODIUM CITRATE; SUCRALOSE; XANTHAN GUM

BACZOL EXPECTORANT (Lex)

Drug Facts

Active ingredients (in each 5 mL tsp.)
Guaifenesin 200 mg

Phenylephrine HCl 5 mg

Purpose
Guaifenesin .....................Expectorant

Phenylephrine ........Nasal Decongestant

INDICATIONS AND USAGE

Uses • helps loosen phlegm (mucus) and thin bronchial secretions to drain

bronchial tubes • temporarily relieves nasal congestion due to the common cold.

Warnings: • Do not exceed recommended dosage • If nervousness,
dizziness, or sleeplessness occurs, discontinue use and consult a
doctor.

Do not use this product • for persistant or chronic cough, such as
occurs with smoking, asthma, chronic bronchitis, or emphysema, or if
cough is accompanied by excessive phlegm (mucus), unless directed
by a Doctor • if you are now taking a prescription Monoamineoxidase
Inhibitor (MAOI) (certain drugs for depression, psychiatric or emotional
conditions, or Parkinson's disease), or for 2 weeks after stopping the
MAOI drug. If you do not know if you are taking a prescription drug that
contains an MAOI, ask a doctor or a pharmacist before taking this product.
• if you have heart disease, high blood pressure, thyroid disease, diabetes,
or difficulty in urination due to enlargement of the prostate gland unless
directed by a Doctor.

Stop use and ask a Doctor • A persistent cough may be a sign of a
serious condition; • If cough persists for more than one week, tend to
recur, or is accompanied by fever, rash or persistent headache; • if
symptoms do not improve within 7 days or are accompanied by fever.

PREGNANCY OR BREAST FEEDING

If pregnant or breast-feeding, ask a health professional before use.

Keep out of reach of children.

In case of overdose, contact a physician or Poison Control Center right away.

DOSAGE AND ADMINISTRATION

Directions Do not exceed more than 6 doses for children and adults
in a 24 - hour period.

Adults and Children; 12 years of age and over | 2 teaspoonfuls (10 mL); every 4 hours
Children 6 to under; 12 years of age | 1 teaspoonful (5 mL); every 4 hours
Children under 6 years of age | Ask a doctor

Other information • Store at room temperature 15º-30ºC (59º-86ºF).
Tamper evident: Do not use if there is evidence of tampering.

INACTIVE INGREDIENT

Inactive ingredients: citric acid, glycerin, garpe flavor, methylparaben

(as preservative), propylene glycol, propylparaben (as preservative),

purified water, sodium citrate, sucralose, xanthan gum

Questions or Comments?

customer.service@lablopez.com.sv

Product Labeling

NDC 76864-209-02

Baczol®
EXPECTORANT

Guaifenesin • Expectorant
Phenylephrine HCl • Nasal Decongestant

Fruit Flavor

• Sugar FREE

• Alcohol FREE

4 fl. oz.

Manufactured For: Laboratorios López, S.A. de C.V.
Boulevard del Ejército Nacional, Km. 5 1/2,
Soyapango, San Salvador,, El Salvador, C.A.

Lot: Rev. 07/2020

Exp. Date:

Carton

Bottle

res